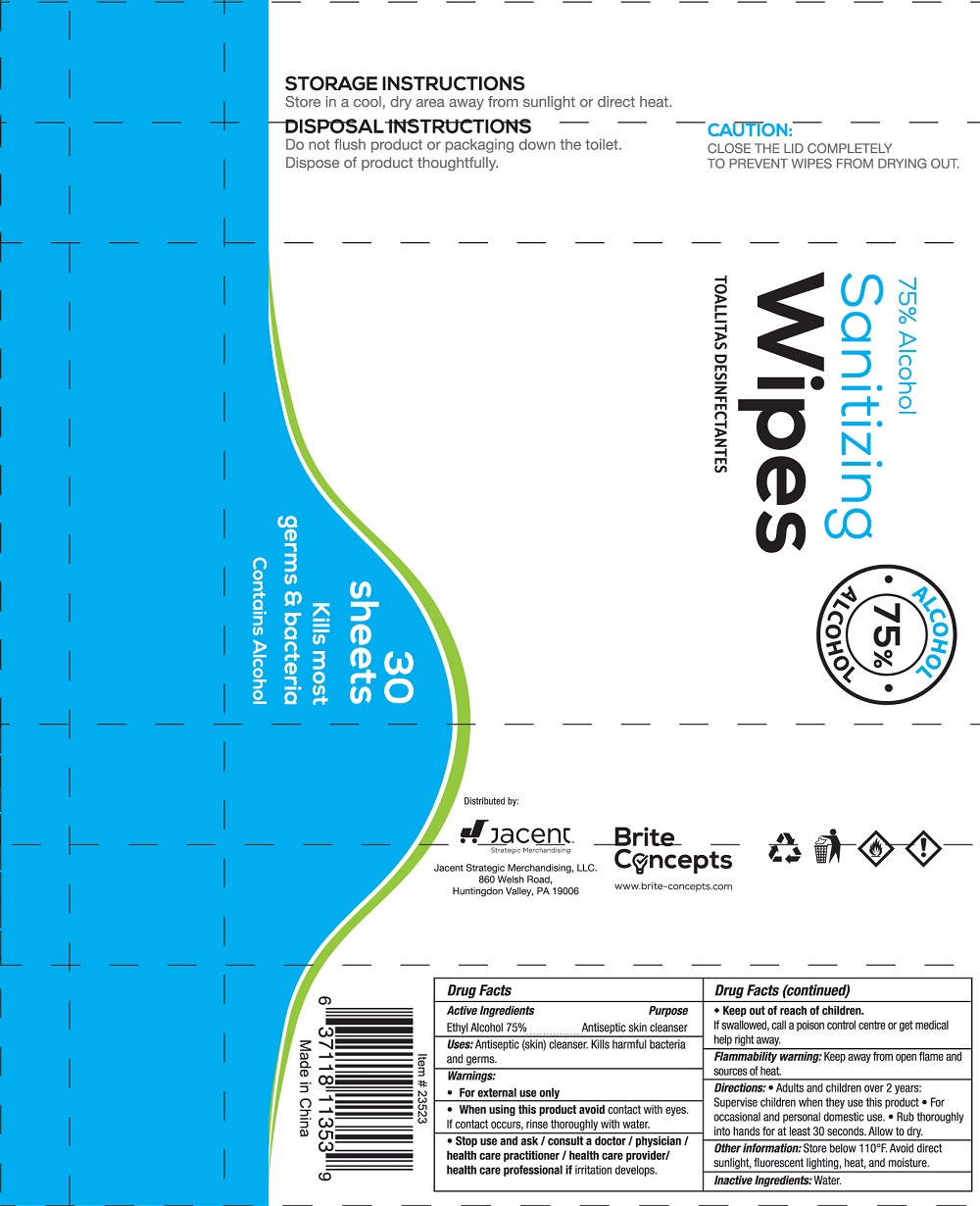 DRUG LABEL: Sanitizing Wipes
NDC: 73326-102 | Form: CLOTH
Manufacturer: JACENT STRATEGIC MERCHANDISING LLC
Category: otc | Type: HUMAN OTC DRUG LABEL
Date: 20200605

ACTIVE INGREDIENTS: ALCOHOL 75 mL/100 mL
INACTIVE INGREDIENTS: WATER

73326-102 sanitizing wipes 75% Alcohol

Active Ingredients

Ethy| Alcohol 75%

PURPOSE

Antiseptic skin cleanser

USE

Antiseptic (skin) cleanser. Kills harmful bacteria and germs.

Warning

●For external use only
●When using this product avoid contact with eyes.
If contact occurs, rinse thoroughly with water,
●Stop use and ask / consult a doctor / physician 1
health care practitioner / health care provider/
health care professional if irritation develops.

KEEP OUT OF REACH OF CHILDREN

If swallowed, call a poison control centre or get medical
help right away.
Flammability warning: Keep away from open flame and
sources of heat.

Directions

Directions:●Adults and children over 2 years:
Supervise children when they use this product●For
occasional and personal domestic use.●Rub thoroughly
into hands for at least 30 seconds. Allow to dry.

Inactive ingredients

Water